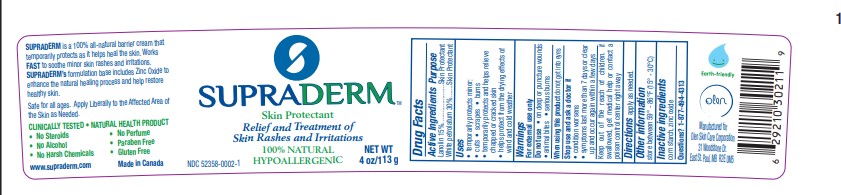 DRUG LABEL: SUPRADERM
NDC: 52358-0002 | Form: CREAM
Manufacturer: Olen Skin Care Corporation
Category: otc | Type: HUMAN OTC DRUG LABEL
Date: 20231001

ACTIVE INGREDIENTS: PETROLATUM 0.3 g/1 g; LANOLIN 0.15 g/1 g
INACTIVE INGREDIENTS: ZINC OXIDE; STARCH, CORN

SUPRADERM

Drug Facts

Active ingredients

Lanolin 15%

White Petrolatum 30%

Purpose

Skin Protectant

Uses

Temporarily Protects Minor:

- Cuts
- Scrapes
- Burns
- Temporarily protects and helps relieve chapped or cracked skin
- Helps protect from the drying effects of wind and cold weather

Warnings

For External Use Only

Do not use

- on deep or puncture wounds
- animal bites
- serious burns

When using this product do not get into eyes

Stop use and ask a doctor if

- condition worsens
- symptoms last more than 7 days or clear up and occur again within a few days

KEEP OUT OF REACH OF CHILDREN

Keep out of the reach of chilren. If swallowed, get mdical help or contact a poison control center right away.

Directions

Apply as needed.

Other information

Store between 59°-86°F (1°5-30°C)

Inactive ingredients

corn starch, zinc oxide

Questions? 1-877-494-4313

PACKAGE LABEL

SUPRADERM

Skin Protectant

Relief and Treatment of

Skin Rashes and Irritations

100% NATURAL

HYPOALLERGENIC

NDC 52358-0002-1

NET WT 4 OZ./113g

Manufactured for

Olen Skin Care Corporation

31 Woodstone Dr

East St. Paul, MB R2E 0M5

Made in Canada